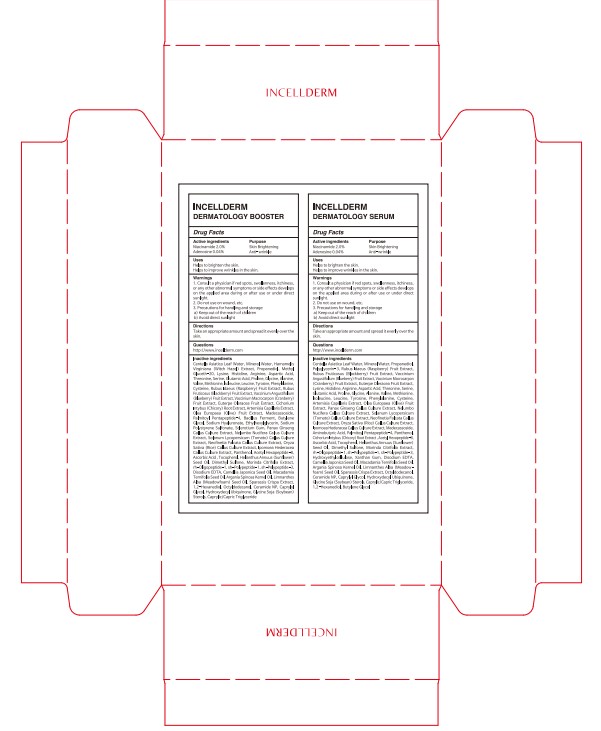 DRUG LABEL: INCELLDERM DERMATOLOGY FIRST PACKAGE
NDC: 72650-080 | Form: KIT | Route: TOPICAL
Manufacturer: Riman Co., Ltd.
Category: otc | Type: HUMAN OTC DRUG LABEL
Date: 20200820

ACTIVE INGREDIENTS: Niacinamide 2.4 g/120 mL; Adenosine 0.048 g/120 mL; Niacinamide 0.9 g/45 mL; Adenosine 0.018 g/45 mL
INACTIVE INGREDIENTS: CENTELLA ASIATICA LEAF; WATER; CENTELLA ASIATICA LEAF; WATER

ACTIVE INGREDIENTS

Niacinamide 2.0%
Adenosine 0.04%

INACTIVE INGREDIENTS

[INCELLDERM DERMATOLOGY BOOSTER]

Centella Asiatica Leaf Water, Mineral Water, Hamamelis Virginiana (Witch Hazel) Extract, Propanediol, Methyl Gluceth-20, Lysine, Histidine, Arginine, Aspartic Acid, Threonine, Serine, Glutamic Acid, Proline, Glycine, Alanine, Valine, Methionine, lsoleucine, Leucine, Tyrosine, Phenylalanine, Cysteine, Rubus Idaeus (Raspberry) Fruit Extract, Rubus Fruticosus (Blackberry) Fruit Extract, Vaccinium Angustifolium (Blueberry) Fruit Extract, Vaccinium Macrocarpon (Cranberry) Fruit Extract, Euterpe Oleracea Fruit Extract, Cichorium Intybus (Chicory) Root Extract, Artemisia Capillaris Extract, Olea Europaea (Olive) Fruit Extract, Madecassoside, Palmitoyl Pentapeptide-4, Bacillus Ferment, Butylene Glycol, Sodium Hyaluronate, Ethylhexylglycerin, Sodium Polystyrene Sulfonate, Sclerotium Gum, Panax Ginseng Callus Culture Extract, Nelumbo Nucifera Callus Culture Extract, Solanum Lycopersicum (Tomato) Callus Culture Extract, Neofinetia Falcata Callus Culture Extract, Oryza Sativa (Rice) Callus Culture Extract, Ipomoea Hederacea Callus Culture Extract, Panthenol, Acetyl Hexapeptide-8, Ascorbic Acid , Tocopherol, Helianthus Annuus (Sunflower) Seed Oil, Dimethyl Sulfone, Morinda Citrifolia Extract, rh-Oligopeptide-1, sh-Polypeptide-1, sh-Polypeptide-3, Disodium EDTA, Camellia Japonica Seed Oil, Macadamia Ternifolia Seed Oil, Argania Spinosa Kernel Oil, Limnanthes Alba (Meadowfoam) Seed Oil, Sparassis Crispa Extract, 1,2-Hexanediol, Octyldodecanol, Ceramide NP, Caprylyl Glycol, Hydroxydecyl Ubiquinone, Glycine Soja (Soybean) Sterols, Caprylic/Capric Triglyceride

[INCELLDERM DERMATOLOGY SERUM]

Centella Asiatica Leaf Water, Mineral Water, Propanediol, Polyglycerin-3, Rubus Idaeus (Raspberry) Fruit Extract, Rubus Fruticosus (Blackberry) Fruit Extract, Vaccinium Angustifolium (Blueberry) Fruit Extract, Vaccinium Macrocarpon (Cranberry) Fruit Extract, Euterpe Oleracea Fruit Extract, Lysine, Histidine, Arginine, Aspartic Acid, Threonine, Serine, Glutamic Acid, Proline, Glycine, Alanine, Valine, Methionine, lsoleucine, Leucine, Tyrosine, Phenylalanine, Cysteine, Artemisia Capillaris Extract, Olea Europaea (Olive) Fruit Extract, Panax Ginseng Callus Culture Extract, Nelumbo Nucifera Callus Culture Extract, Solanum Lycopersicum (Tomato) Callus Culture Extract, Neofinetia Falcata Callus Culture Extract, Oryza Sativa (Rice) Callus Culture Extract, Ipomoea Hederacea Callus Culture Extract, Madecassoside, Aminobutyric Acid, Palmitoyl Pentapeptide-4, Panthenol, Cichorium Intybus (Chicory) Root Extract , Acetyl Hexapeptide-8, Ascorbic Acid, Tocopherol, Helianthus Annuus (Sunflower) Seed Oil, Dimethyl Sulfone, Morinda Citrifolia Extract, rh-Oligopeptide-1, sh-Polypeptide-1, sh-Polypeptide-3, Hydroxyethylcellulose, Xanthan Gum, Disodium EDTA, Camellia Japonica Seed Oil, Macadamia Ternifolia Seed Oil, Argania Spinosa Kernel Oil, Limnanthes Alba (Meadowfoam) Seed Oil, Sparassis Crispa Extract, Octyldodecanol, Ceramide NP, Caprylyl Glycol, Hydroxydecyl Ubiquinone, Glycine Soja (Soybean) Sterols, Caprylic/Capric Triglyceride, 1,2-Hexanediol, Butylene Glycol

PURPOSE

Skin Brightening
Anti-wrinkle

WARNINGS

1. Consult a physician if red spots, swollenness, itchiness, or any other abnormal symptoms or side effects develops on the applied area during or after use or under direct sunlight.
2. Do not use on wound, etc.
3. Precautions for handling and storage
a) Keep out of the reach of children
b) Avoid direct sunlight

KEEP OUT OF REACH OF CHILDREN

Uses

Helps to brighten the skin.
Helps to improve wrinkles in the skin.

Directions

Take an appropriate amount and spread it evenly over the skin.

QUESTIONS

http://www.incellderm.com